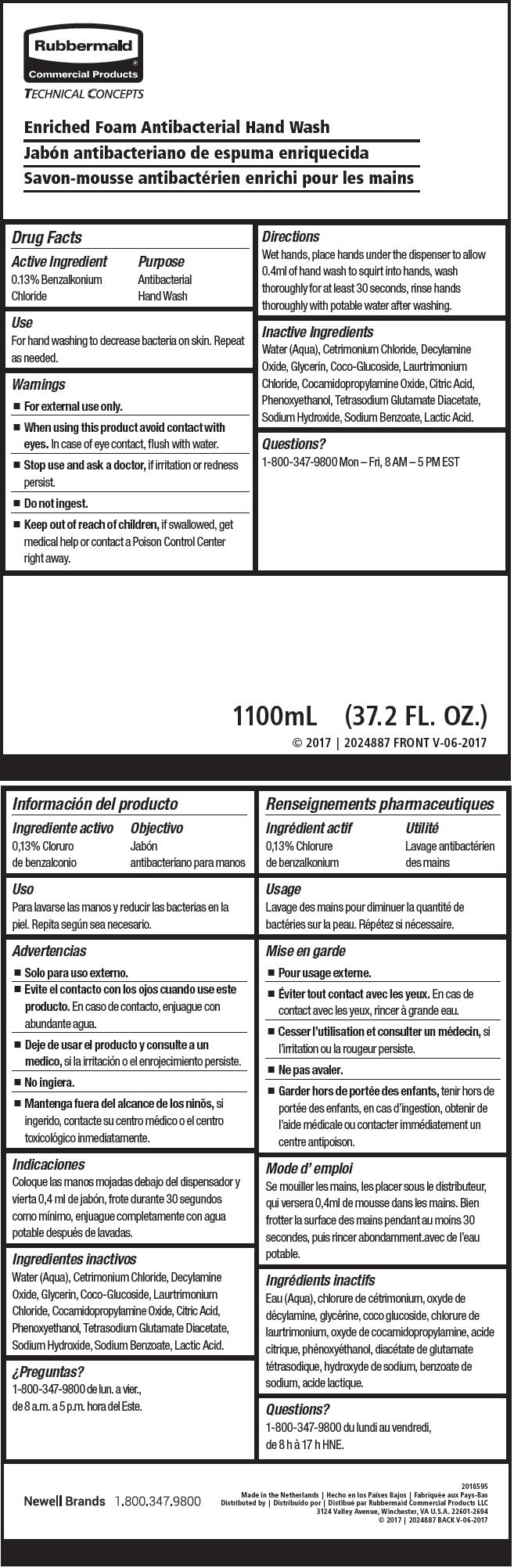 DRUG LABEL: Antibacterial Hand Wash
NDC: 65321-032 | Form: SOAP
Manufacturer: Rubbermaid Commercial Products LLC
Category: otc | Type: HUMAN OTC DRUG LABEL
Date: 20231218

ACTIVE INGREDIENTS: BENZALKONIUM CHLORIDE 13 mg/10 mL
INACTIVE INGREDIENTS: WATER; CETRIMONIUM CHLORIDE; DECYLAMINE OXIDE; GLYCERIN; COCO GLUCOSIDE; LAURTRIMONIUM CHLORIDE; COCAMIDOPROPYLAMINE OXIDE; CITRIC ACID MONOHYDRATE; PHENOXYETHANOL; TETRASODIUM GLUTAMATE DIACETATE; SODIUM HYDROXIDE; SODIUM BENZOATE; LACTIC ACID, UNSPECIFIED FORM

Enriched Foam Antibacterial Hand Wash

Drug Facts

Active Ingredient

0.13% Benzalkonium Chloride

Purpose

Antibacterial Hand Wash

Use

For hand washing to decrease bacteria on skin. Repeat as needed.

Warnings

- For external use only.

- When using this product avoid contact with eyes. In case of eye contact, flush with water.

- Stop use and ask a doctor, if irritation or redness persist.

- Do not ingest.

- Keep out of reach of children, if swallowed, get medical help or contact a Poison Control Center right away.

Directions

Wet hands, place hands under the dispenser to allow 0.4ml of hand wash to squirt into hands, wash thoroughly for at least 30 seconds, rinse hands thoroughly with potable water after washing.

Inactive Ingredients

Water (Aqua), Cetrimonium Chloride, Decylamine Oxide, Glycerin, Coco-Glucoside, Laurtrimonium Chloride, Cocamidopropylamine Oxide, Citric Acid, Phenoxyethanol, Tetrasodium Glutamate Diacetate, Sodium Hydroxide, Sodium Benzoate, Lactic Acid.

Questions?

1-800-347-9800 Mon – Fri, 8 AM – 5 PM EST

Distributed by Rubbermaid Commercial Products LLC
3124 Valley Avenue, Winchester, VA U.S.A. 22601-2694

PRINCIPAL DISPLAY PANEL - 1100 mL Bag Label

Rubbermaid®
Commercial Products

TECHNICAL CONCEPTS

Enriched Foam Antibacterial Hand Wash

1100mL (37.2 FL. OZ.)
© 2017 | 2024887 FRONT V-06-2017